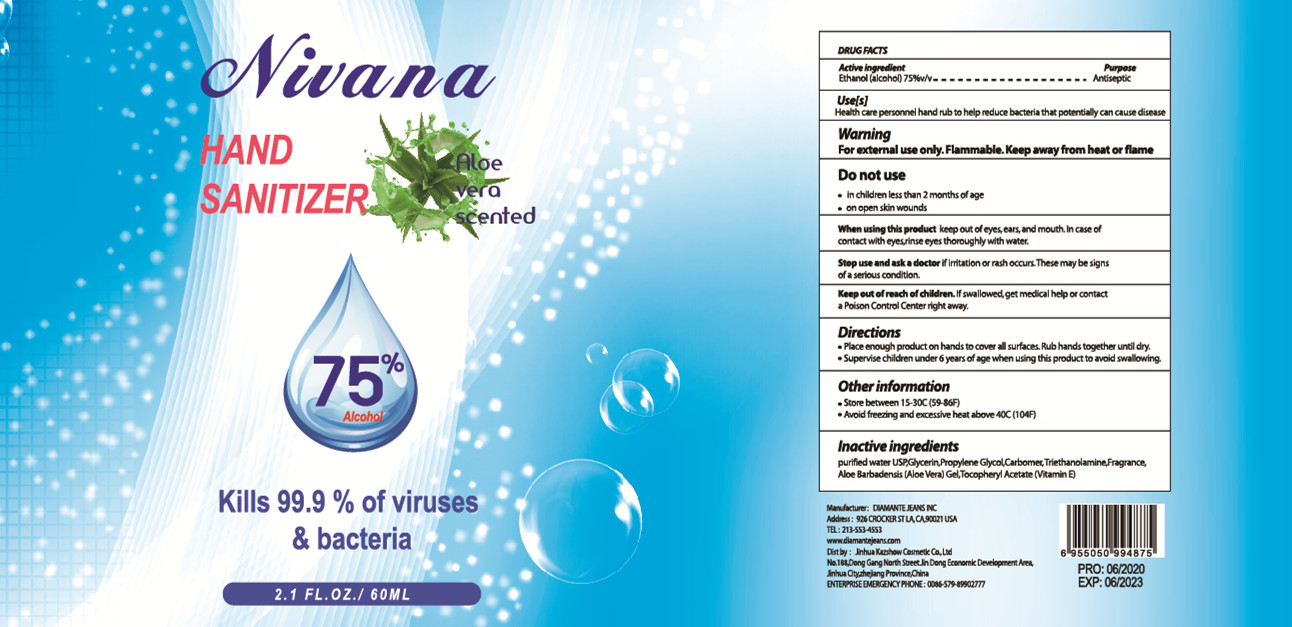 DRUG LABEL: Nivana HAND SANITIZER
NDC: 54248-004 | Form: GEL
Manufacturer: JINHUA KAZSHOW COSMETICS CO., LTD.
Category: otc | Type: HUMAN OTC DRUG LABEL
Date: 20200611

ACTIVE INGREDIENTS: ALCOHOL 45 mL/60 mL
INACTIVE INGREDIENTS: GLYCERIN; FRAGRANCE LAVENDER & CHIA F-153480; ALOE VERA LEAF; PROPYLENE GLYCOL; WATER; TROLAMINE; .ALPHA.-TOCOPHEROL ACETATE; CARBOMER HOMOPOLYMER, UNSPECIFIED TYPE

DOSAGE AND ADMINISTRATION

●Store between 15-30°C(59-86°F)
●Avoid freezing and excessive heat above 40°C (104°F)

INACTIVE INGREDIENT

Purified water USP, Glycerin, Propylene Glycol, Carbomer, Triethanolamine, Fragrance ,Aloe Barbadensis (Aloe Vera) Gel ，Tocopheryl Acetate (Vitamin E)

INDICATIONS AND USAGE

●Place enough product on hands to cover all surfaces. Rub hands together until dry.
●Supervise children under 6 years of age when using this product to avoid swal lowing.

ACTIVE INGREDIENT

Alcohol

keep out of reach of children

PURPOSE

Disinfection
Sterilization
No Rinseing

WARNINGS

For external use only. Flammable.Keep away from heat or flame